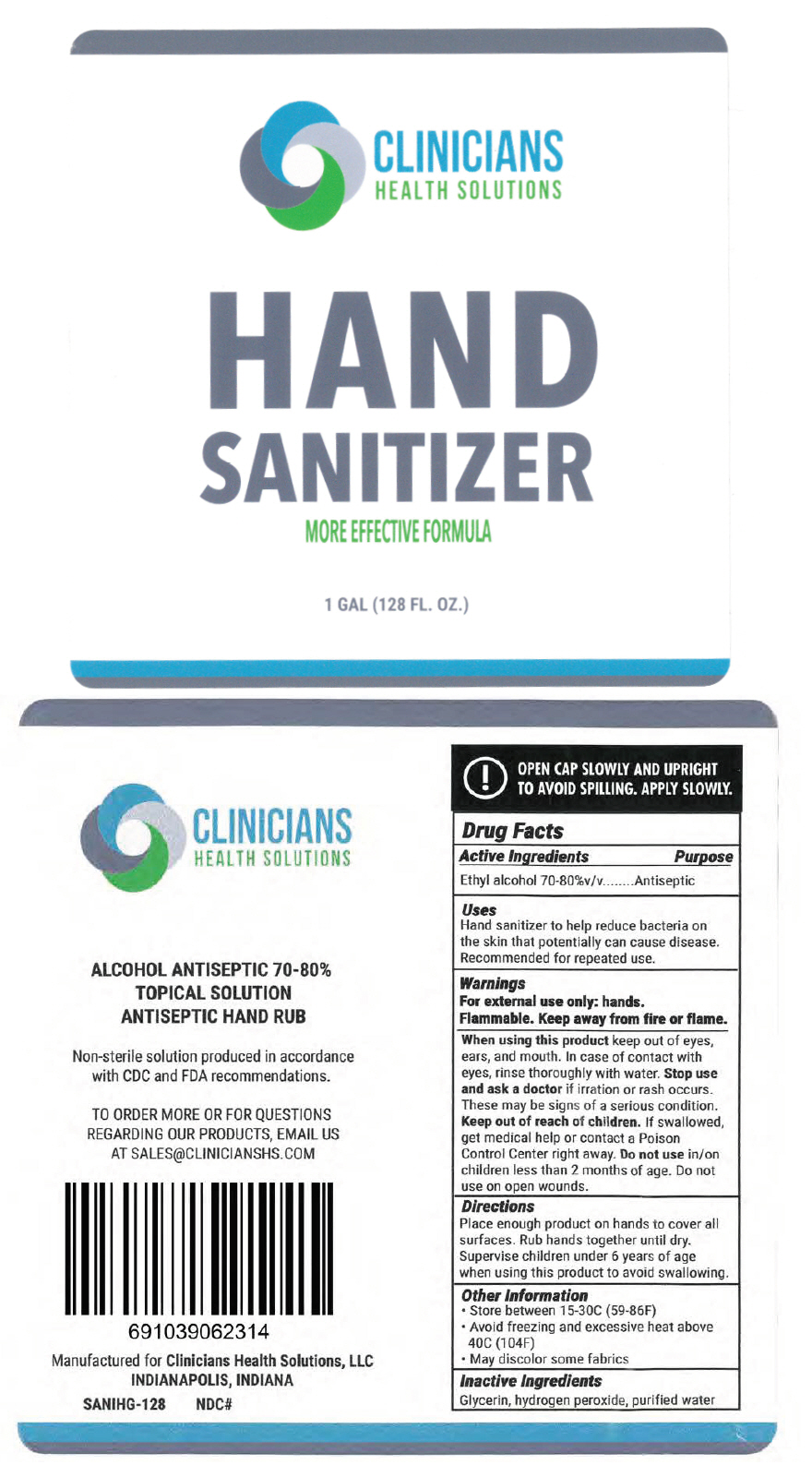 DRUG LABEL: Alcohol Hand Sanitizer
NDC: 72625-600 | Form: SOLUTION
Manufacturer: Pharmaneek Inc.
Category: otc | Type: HUMAN OTC DRUG LABEL
Date: 20200417

ACTIVE INGREDIENTS: ALCOHOL 75 mL/100 mL
INACTIVE INGREDIENTS: Glycerin; hydrogen peroxide; water

Alcohol Hand Sanitizer

Drug Facts

Active Ingredients

Ethyl alcohol 70-80%v/v

Purpose

Antiseptic

Uses

Hand sanitizer to help reduce bacteria on the skin that potentially can cause disease. Recommended for repeated use.

Warnings

For external use only: hands.

Flammable. Keep away from fire or flame.

When using this product keep out of eyes. ears, and mouth. In case of contact with eyes, rinse thoroughly with water. Stop use and ask a doctor if irration or rash occurs. These may be signs of a serious condition.

Keep out of reach of children. If swallowed, get medical help or contact a Poison Control Center right away. Do not use in/on children less than 2 months of age. Do not use on open wounds.

Directions

Place enough product on hands to cover all surfaces. Rub hands together until dry. Supervise children under 6 years of age when using this product to avoid swallowing.

Other Information

- Store between 15-30C (59-86F)
- Avoid freezing and excessive heat above 40C (104F)
- May discolor some fabrics

Inactive Ingredients

Glycerin. hydrogen peroxide, purified water

QUESTIONS

TO ORDER MORE OR FOR QUESTIONS REGARDING OUR PRODUCTS, EMAIL US AT SALES@CLINICIANSHS.COM

PRINCIPAL DISPLAY PANEL - 1 GAL Bottle Label

CLINICIANS
HEALTH SOLUTIONS

HAND
SANITIZER
MORE EFFECTIVE FORMULA

1 GAL (128 FL. OZ.)